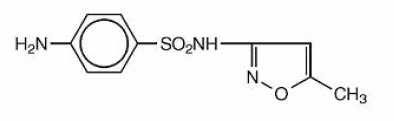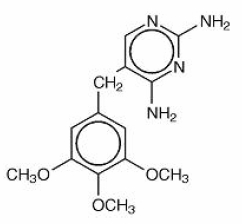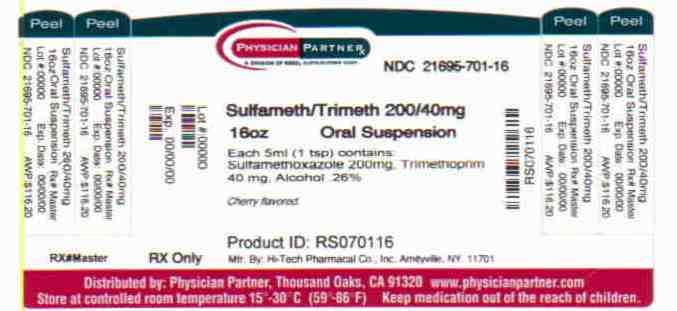 DRUG LABEL: Sulfamethoxazole and Trimethoprim
NDC: 21695-701 | Form: SUSPENSION
Manufacturer: Rebel Distributors Corp
Category: prescription | Type: HUMAN PRESCRIPTION DRUG LABEL
Date: 20101201

ACTIVE INGREDIENTS: SULFAMETHOXAZOLE 200 mg/5 mL; TRIMETHOPRIM 40 mg/5 mL
INACTIVE INGREDIENTS: ALCOHOL; METHYLPARABEN; SODIUM BENZOATE; CARBOXYMETHYLCELLULOSE SODIUM; ANHYDROUS CITRIC ACID; GLYCERIN; CELLULOSE, MICROCRYSTALLINE; POLYSORBATE 80; WATER; SACCHARIN SODIUM; SORBITOL; FD&C RED NO. 40; FD&C YELLOW NO. 6; CHERRY

Sulfamethoxazole and Trimethoprim Oral Suspension, USP

To reduce the development of drug-resistant bacteria and maintain the effectiveness of sulfamethoxazole and trimethoprim oral suspension and other antibacterial drugs, sulfamethoxazole and trimethoprim oral suspension should be used only to treat or prevent infections that are proven or strongly suspected to be caused by bacteria.

DESCRIPTION

Sulfamethoxazole and Trimethoprim Oral Suspension USP is a synthetic antibacterial combination product. Sulfamethoxazole is N^1-(5-methyl-3-isoxazolyl) sulfanilamide. It is an almost white, odorless, tasteless compound. It has the following structural formula is:

C10H11N3O3S M.W. 253.28

Trimethoprim is 2,4-diamino-5-(3,4,5- trimethoxybenzyl) pyrimidine. It is a white to light yellow, odorless, bitter compound. It has the following structural formula is:

C14H18N4O3 M.W. 290.32

Each teaspoonful (5 mL) for oral administration, contains 200 mg sulfamethoxazole and 40 mg trimethoprim in a vehicle containing alcohol 0.26%, methylparaben 0.1% and sodium benzoate 0.1% (added as preservatives), carboxymethylcellulose sodium, citric acid (anhydrous), glycerin, microcrystalline cellulose, polysorbate 80, purified water, saccharin sodium, and sorbitol. The light purple, grape flavored suspension contains the following additional inactive ingredients: FD&C Red No. 40, FD&C Blue No. 1 and natural and artificial grape flavor. The pink, cherry flavored suspension contains the following additional inactive ingredients: FD&C Red No. 40, FD&C Yellow No. 6 and artificial cherry flavor.

CLINICAL PHARMACOLOGY

Sulfamethoxazole and trimethoprim oral suspension is rapidly absorbed following oral administration. Both sulfamethoxazole and trimethoprim exist in the blood as unbound, protein-bound, and metabolized forms; sulfamethoxazole also exists as the conjugated form. The metabolism of sulfamethoxazole occurs predominantly by N4-acetylation although the glucuronide conjugate has been identified. The principal metabolites of trimethoprim are the 1- and 3-oxides and the 3’- and 4’-hydroxy derivatives. The free forms of sulfamethoxazole and trimethoprim are considered to be the therapeutically active forms. Approximately 44% of trimethoprim and 70% of sulfamethoxazole are bound to plasma proteins. The presence of 10 mg percent sulfamethoxazole in plasma decreases the protein binding of trimethoprim by an insignificant degree; trimethoprim does not influence the protein binding of sulfamethoxazole. Peak blood levels for the individual components occur 1 to 4 hours after oral administration. The mean serum half-lives of sulfamethoxazole and trimethoprim are 10 and 8 to 10 hours, respectively. However, patients with severely impaired renal function exhibit an increase in the half-lives of both components, requiring dosage regimen adjustment (see DOSAGE AND ADMINISTRATION). Detectable amounts of trimethoprim and sulfamethoxazole are present in the blood 24 hours after drug administration. During administration of 160 mg trimethoprim and 800 mg sulfamethoxazole b.i.d., the mean steady-state plasma concentration of trimethoprim was 1.72 mcg/mL. The steady-state minimal plasma levels of free and total sulfamethoxazole were 57.4 mcg/mL and 68.0 mcg/mL, respectively. These steady-state levels were achieved after 3 days of drug administration.^1

Excretion of sulfamethoxazole and trimethoprim is primarily by the kidneys through both glomerular filtration and tubular secretion. Urine concentrations of both sulfamethoxazole and trimethoprim are considerably higher than are the concentrations in the blood. The average percentage of the dose recovered in urine from 0 to 72 hours after a single oral dose is 84.5% for total sulfonamide and 66.8% for free trimethoprim. Thirty percent of the total sulfonamide is excreted as free sulfamethoxazole, with the remaining as N4-acetylated metabolite.2 When administered together, neither sulfamethoxazole nor trimethoprim affects the urinary excretion pattern of the other.

Both sulfamethoxazole and trimethoprim distribute to sputum, vaginal fluid, and middle ear fluid; trimethoprim also distributes to bronchial secretions, and both pass the placental barrier and are excreted in human milk.

Geriatric Pharmacokinetics

The pharmacokinetics of sulfamethoxazole 800 mg and trimethoprim 160 mg were studied in 6 geriatric subjects (mean age: 78.6 years) and 6 young healthy subjects (mean age: 29.3 years) using a non-U.S. approved formulation. Pharmacokinetic values for sulfamethoxazole in geriatric subjects were similar to those observed in young adult subjects. The mean renal clearance of trimethoprim was significantly lowered in geriatric subjects compared with young adult subjects (19 mL/h/kg vs. 55 mL/h/kg). However, after normalizing by body weight, the apparent total body clearance of trimethoprim was an average 19% lower in geriatric subjects compared with young adult subjects.^3

Microbiology

Sulfamethoxazole inhibits bacterial synthesis of dihydrofolic acid by competing with para-aminobenzoic acid (PABA). Trimethoprim blocks the production of tetrahydrofolic acid from dihydrofolic acid by binding to and reversibly inhibiting the required enzyme, dihydrofolate reductase. Thus, this combination blocks two consecutive steps in the biosynthesis of nucleic acids and proteins essential to many bacteria.

In vitro studies have shown that bacterial resistance develops more slowly with this combination than with either sulfamethoxazole or trimethoprim alone.

In vitro serial dilution tests have shown that the spectrum of antibacterial activity of sulfamethoxazole and trimethoprim includes the common urinary tract pathogens with the exception of Pseudomonas aeruginosa. The following organisms are usually susceptible: Escherichia coli, Klebsiella species, Enterobacter species, Morganella morganii, Proteus mirabilis and indole-positive Proteus species including Proteus vulgaris.

The usual spectrum of antimicrobial activity of sulfamethoxazole and trimethoprim includes bacterial pathogens isolated from middle ear exudate and from bronchial secretions (Haemophilus influenzae, including ampicillin-resistant strains, and Streptococcus pneumoniae), enterotoxigenic strains of Escherichia coli (ETEC) causing bacterial gastroenteritis. Shigella flexneri and Shigella sonnei are also usually susceptible.

REPRESENTATIVE MINIMUM INHIBITORY CONCENTRATION VALUES FOR ORGANISMS SUSCEPTIBLE TO SULFAMETHOXAZOLE AND TRIMETHOPRIM (MIC - mcg/mL)
Bacteria |  |  | TMP/SMX (1:19)
Bacteria | TMP Alone | SMX Alone | TMP | SMX
Escherichia coli | 0.05 to 1.5 | 1.0 to 245 | 0.05 to 0.5 | 0.95 to 9.5
Escherichia coli (enterotoxigenic strains) | 0.015 to 0.15 | 0.285 to > 950 | 0.005 to 0.15 | 0.095 to 2.85
Proteus species (indole positive) | 0.5 to 5.0 | 7.35 to 300 | 0.05 to 1.5 | 0.95 to 28.5
Morganella morganii | 0.5 to 5.0 | 7.35 to 300 | 0.05 to 1.5 | 0.95 to 28.5
Proteus mirabilis | 0.5 to 1.5 | 7.35 to 30 | 0.05 to 0.15 | 0.95 to 2.85
Klebsiella species | 0.15 to 5.0 | 2.45 to 245 | 0.05 to 1.5 | 0.95 to 28.5
Enterobacter species | 0.15 to 5.0 | 2.45 to 245 | 0.05 to 1.5 | 0.95 to 28.5
Haemophilus influenzae | 0.15 to 1.5 | 2.85 to 95 | 0.015 to 0.15 | 0.285 to 2.85
Streptococcus pneumoniae | 0.15 to 1.5 | 7.35 to 24.5 | 0.05 to 0.15 | 0.95 to 2.85
Shigella flexneri* [*Rudoy RC, Nelson JD, Haltalin KC. Antimicrobial Agents and Chemotherapy. 1974;5:439-443.] | < 0.01 to 0.04 | < 0.16 to > 320 | < 0.002 to 0.03 | 0.04 to 0.625
Shigella sonnei* | 0.02 to 0.08 | 0.625 to > 320 | 0.004 to 0.06 | 0.08 to 1.25

TMP = trimethoprim

SMX = sulfamethoxazole

Susceptibility Testing: The recommended quantitative disc susceptibility method may be used for estimating the susceptibility of bacteria to sulfamethoxazole and trimethoprim. ^(3, 4) With this procedure, a report from the laboratory of “Susceptible to trimethoprim and sulfamethoxazole” indicates that the infection is likely to respond to therapy with this product. If the infection is confined to the urine, a report of “Intermediate susceptibility to trimethoprim and sulfamethoxazole” also indicates that the infection is likely to respond. A report of “Resistant to trimethoprim and sulfamethoxazole” indicates that the infection is unlikely to respond to therapy with this product.

INDICATIONS AND USAGE

To reduce the development of drug-resistant bacteria and maintain the effectiveness of sulfamethoxazole and trimethoprim oral suspension and other antibacterial drugs, sulfamethoxazole and trimethoprim oral suspension should be used only to treat or prevent infections that are proven or strongly suspected to be caused by susceptible bacteria. When culture and susceptibility information are available, they should be considered in selecting or modifying antibacterial therapy. In the absence of such data, local epidemiology and susceptibility patterns may contribute to the empiric selection of therapy.

URINARY TRACT INFECTIONS

For the treatment of urinary tract infections due to susceptible strains of the following organisms: Escherichia coli, Klebsiella species, Enterobacter species, Morganella morganii, Proteus mirabilis, and Proteus vulgaris. It is recommended that initial episodes of uncomplicated urinary tract infections be treated with a single effective antibacterial agent rather than the combination.

ACUTE OTITIS MEDIA

For the treatment of acute otitis media in pediatric patients due to susceptible strains of Streptococcus pneumoniae or Haemophilus influenzae when, in the judgment of the physician, sulfamethoxazole and trimethoprim oral suspension offers some advantage over the use of other antimicrobial agents. To date, there are limited data on the safety of repeated use of sulfamethoxazole and trimethoprim in pediatric patients under two years of age. This product is not indicated for prophylactic or prolonged administration in otitis media at any age.

ACUTE EXACERBATIONS OF CHRONIC BRONCHITIS IN ADULTS

For the treatment of acute exacerbations of chronic bronchitis due to susceptible strains of Streptococcus pneumoniae or Haemophilus influenzae when, in the judgment of the physician, sulfamethoxazole and trimethoprim oral suspension offers some advantage over the use of a single antimicrobial agent.

TRAVELERS’ DIARRHEA IN ADULTS

For the treatment of travelers’ diarrhea due to susceptible strains of enterotoxigenic E. coli.

SHIGELLOSIS

For the treatment of enteritis caused by susceptible strains of Shigella flexneri and Shigella sonnei when antibacterial therapy is indicated.

PNEUMOCYSTIS CARINII PNEUMONIA

For the treatment of documented Pneumocystis carinii pneumonia. For prophylaxis against Pneumocystis carinii pneumonia in individuals who are immunosuppressed and considered to be at an increased risk of developing Pneumocystis carinii pneumonia.

CONTRAINDICATIONS

Sulfamethoxazole and trimethoprim oral suspension is contraindicated in patients with a known hypersensitivity to trimethoprim or sulfonamides and in patients with documented megaloblastic anemia due to folate deficiency. Sulfamethoxazole and trimethoprim oral suspension is also contraindicated in pregnant patients at term and in nursing mothers, because sulfonamides pass the placenta and are excreted in the milk and may cause kernicterus. Sulfamethoxazole and trimethoprim oral suspension is contraindicated in pediatric patients less than two months of age.

WARNINGS

FATALITIES ASSOCIATED WITH THE ADMINISTRATION OF SULFONAMIDES, ALTHOUGH RARE, HAVE OCCURRED DUE TO SEVERE REACTIONS, INCLUDING STEVENS-JOHNSON SYNDROME, TOXIC EPIDERMAL NECROLYSIS, FULMINANT HEPATIC NECROSIS, AGRANULOCYTOSIS, APLASTIC ANEMIA, AND OTHER BLOOD DYSCRASIAS.

SULFONAMIDES, INCLUDING SULFONAMIDE-CONTAINING PRODUCTS SUCH AS SULFAMETHOXAZOLE/TRIMETHOPRIM SHOULD BE DISCONTINUED AT THE FIRST APPEARANCE OF SKIN RASH OR ANY SIGN OF ADVERSE REACTION. In rare instances, a skin rash may be followed by a more severe reaction, such as Stevens-Johnson syndrome, toxic epidermal necrolysis, hepatic necrosis and serious blood disorder (see PRECAUTIONS).

Clinical signs, such as rash, sore throat, fever, arthralgia, pallor, purpura, or jaundice may be early indications of serious reactions.

Cough, shortness of breath, and pulmonary infiltrates are hypersensitivity reactions of the respiratory tract that have been reported in association with sulfonamide treatment.

The sulfonamides should not be used for the treatment of group A beta-hemolytic streptococcal infections. In an established infection, they will not eradicate the streptococcus and, therefore, will not prevent sequelae such as rheumatic fever.

Clostridium difficile associated diarrhea (CDAD) has been reported with use of nearly all antibacterial agents, including sulfamethoxazole and trimethoprim oral suspension, USP, and may range in severity from mild diarrhea to fatal colitis. Treatment with antibacterial agents alters the normal flora of the colon leading to overgrowth of C. difficile.

C. difficile produces toxins A and B which contribute to the development of CDAD. Hypertoxin producing strains of C. difficile cause increased morbidity and mortality, as these infections can be refractory to antimicrobial therapy and may require colectomy. CDAD must be considered in all patients who present with diarrhea following antibiotic use. Careful medical history is necessary since CDAD has been reported to occur over two months after the administration of antibacterial agents.

If CDAD is suspected or confirmed, ongoing antiobiotic use not directed against C. difficile may need to be discontinued. Appropriate fluid and electrolyte management, protein supplementation, antibiotic treatment of C. difficile, and surgical evaluation should be instituted as clinically indicated.

PRECAUTIONS

General

Prescribing sulfamethoxazole and trimethoprim oral suspension in the absence of a proven or strongly suspected bacterial infection or a prophylactic indication is unlikely to provide benefit to the patient and increases the risk of the development of drug-resistant bacteria. Sulfamethoxazole and trimethoprim oral suspension should be given with caution to patients with impaired renal or hepatic function, to those with possible folate deficiency (e.g., the elderly, chronic alcoholics, patients receiving anticonvulsant therapy, patients with malabsorption syndrome, and patients in malnutrition states), and to those with severe allergy or bronchial asthma. In glucose-6-phosphate dehydrogenase-deficient individuals, hemolysis may occur. This reaction is frequently dose-related (see CLINICAL PHARMACOLOGYand DOSAGE AND ADMINISTRATION).

Use in the Elderly

There may be an increased risk of severe adverse reactions in elderly patients, particularly when complicating conditions exist, e.g., impaired kidney and/or liver function, or concomitant use of other drugs. Severe skin reactions, generalized bone marrow suppression (see WARNINGS and ADVERSE REACTIONS), or a specific decrease in platelets (with or without purpura) are the most frequently reported severe adverse reactions in elderly patients. In those concurrently receiving certain diuretics, primarily thiazides, an increased incidence of thrombocytopenia with purpura has been reported. Appropriate dosage adjustments should be made for patients with impaired kidney function (see DOSAGE AND ADMINISTRATION).

Use in the Treatment of and Prophylaxis for Pneumocystis carinii Pneumonia in Patients with Acquired Immunodeficiency Syndrome (AIDS)

The incidence of side effects, particularly rash, fever, leukopenia, and elevated aminotransferase (transaminase) values in AIDS patients who are being treated with sulfamethoxazole and trimethoprim therapy for Pneumocystis carinii pneumonia has been reported to be greatly increased compared with the incidence normally associated with the use of sulfamethoxazole and trimethoprim in non-AIDS patients. The incidence of hyperkalemia and hyponatremia appears to be increased in AIDS patients receiving sulfamethoxazole and trimethoprim. Adverse effects are generally less severe in patients receiving sulfamethoxazole and trimethoprim for prophylaxis. A history of mild intolerance to sulfamethoxazole and trimethoprim in AIDS patients does not appear to predict intolerance of subsequent secondary prophylaxis. However, if a patient develops skin rash or any sign of adverse reaction, therapy with sulfamethoxazole and trimethoprim should be re-evaluated (see WARNINGS).

The concomitant use of leucovorin with sulfamethoxazole/trimethoprim for the acute treatment of Pneumocystis carinii pneumonia in patients with HIV infection was associated with increased rates of treatment failure and morbidity in a placebo-controlled study.

Information for patients

Patients should be counseled that antibacterial drugs including sulfamethoxazole and trimethoprim oral suspension should only be used to treat bacterial infections. They do not treat viral infections (e.g., the common cold). When sulfamethoxazole and trimethoprim oral suspension is prescribed to treat a bacterial infection, patients should be told that although it is common to feel better early in the course of therapy, the medication should be taken exactly as directed. Skipping doses or not completing the full course of therapy may (1) decrease the effectiveness of the immediate treatment and (2) increase the likelihood that bacteria will develop resistance and will not be treatable by sulfamethoxazole and trimethoprim oral suspension or other antibaceterial drugs in the future.

Patients should be instructed to maintain an adequate fluid intake in order to prevent crystalluria and stone formation.

Diarrhea is a common problem caused by antibiotics which usually ends when the antibiotic is discontinued. Sometimes after starting treatment with antibiotics, patients can develop watery and bloody stools (with and without stomach cramps and fever) even as late as two or more months after having taken the last dose of the antibiotic. If this occurs, patients should contact their physician as soon as possible.

Laboratory tests

Complete blood counts should be done frequently in patients receiving sulfamethoxazole and trimethoprim; if a significant reduction in the count of any formed blood element is noted, sulfamethoxazole and trimethoprim oral suspension should be discontinued. Urinalyses with careful microscopic examination and renal function tests should be performed during therapy, particularly for those patients with impaired renal function.

Drug Interactions

In elderly patients concurrently receiving certain diuretics, primarily thiazides, an increased incidence of thrombocytopenia with purpura has been reported. In the literature, two cases of hyperkalemia in elderly patients have been reported after concomitant intake of sulfamethoxazole/trimethoprim and an angiotensin converting enzyme inhibitor.

It has been reported that sulfamethoxazole and trimethoprim may prolong the prothrombin time in patients who are receiving the anticoagulant warfarin. This interaction should be kept in mind when sulfamethoxazole and trimethoprim is given to patients already on anticoagulant therapy, and the coagulation time should be reassessed.

Sulfamethoxazole and trimethoprim may inhibit the hepatic metabolism of phenytoin. Sulfamethoxazole and trimethoprim, given at a common clinical dosage, increased the phenytoin half-life by 39% and decreased the phenytoin metabolic clearance rate by 27%. When administering these drugs concurrently, one should be alert for possible excessive phenytoin effect.

Sulfonamides can also displace methotrexate from plasma protein binding sites,thus increasing free methotrexate concentrations.

Drug/Laboratory Test Interactions

This combination product, specifically the trimethoprim component, can interfere with a serum methotrexate assay as determined by the competitive binding protein technique (CBPA) when a bacterial dihydrofolate reductase is used as the binding protein. No interference occurs, however, if methotrexate is measured by a radioimmunoassay (RIA).

The presence of trimethoprim and sulfamethoxazole may also interfere with the Jaffé alkaline picrate reaction assay for creatinine, resulting in overestimations of about 10% in the range of normal values.

Carcinogenesis, mutagenesis, impairment of fertility

Carcinogenesis

Long-term studies in animals to evaluate carcinogenic potential have not been conducted with sulfamethoxazole and trimethoprim.

Mutagenesis

Bacterial mutagenic studies have not been performed with sulfamethoxazole and trimethoprim in combination. Trimethoprim was demonstrated to be non-mutagenic in the Ames assay. In studies at two laboratories, no chromosomal damage was detected in cultured Chinese hamster ovary cells at concentration approximately 500 times human plasma levels; at concentrations approximately 1,000 times human plasma levels in these same cells, a low level of chromosomal damage was induced at one of these laboratories. No chromosomal abnormalities were observed in cultured human leukocytes at concentrations of trimethoprim up to 20 times human steady-state plasma levels. No chromosomal effects were detected in peripheral lymphocytes of human subjects receiving 320 mg of trimethoprim in combination with up to 1,600 mg of sulfamethoxazole per day for as long as 112 weeks.

Impairment Of Fertility

No adverse effects on fertility or general reproductive performance were observed in rats given oral dosages as high as 70 mg/kg/day trimethoprim plus 350 mg/kg/day sulfamethoxazole.

Pregnancy

Teratogenic effects

Pregnancy Category C. In rats, oral doses of 533 mg/kg sulfamethoxazole or 200 mg/kg trimethoprim produced teratologic effects manifested mainly as cleft palates. The highest dose which did not cause cleft palates in rats was 512 mg/kg sulfamethoxazole or 192 mg/kg trimethoprim when administered separately. In two studies in rats, no teratogenicity was observed when 512 mg/kg of sulfamethoxazole was used in combination with 128 mg/kg of trimethoprim. In one study, however, cleft palates were observed in one litter out of 9 when 355 mg/kg of sulfamethoxazole was used in combination with 88 mg/kg of trimethoprim.

In some rabbit studies, an overall increase in fetal loss (dead and resorbed and malformed conceptuses) was associated with doses of trimethoprim six times the human therapeutic dose.

While there are no large, well-controlled studies in the use of trimethoprim and sulfamethoxazole in pregnant women, Brumfitt and Pursell,^5 in a retrospective study, reported the outcome of 186 pregnancies during which the mother received either placebo or trimethoprim and sulfamethoxazole. The incidence of congenital abnormalities was 4.5% (3 of 66) in those who received placebo and 3.3% (4 of 120) in those receiving trimethoprim and sulfamethoxazole. There were no abnormalities in the 10 children whose mothers received the drug during the first trimester. In a separate survey, Brumfitt and Pursell also found no congenital abnormalities in 35 children whose mothers had received oral trimethoprim and sulfamethoxazole at the time of conception or shortly thereafter.

Because trimethoprim and sulfamethoxazole may interfere with folic acid metabolism, sulfamethoxazole and trimethoprim oral suspension should be used during pregnancy only if the potential benefit justifies the potential risk to the fetus.

Nonteratogenic effects

See CONTRAINDICATIONS section.

Nursing mothers

See CONTRAINDICATIONS section.

Pediatric use

Sulfamethoxazole and trimethoprim oral suspension is not recommended for pediatric patients younger than 2 months of age (see INDICATIONS AND USAGE and CONTRAINDICATIONS).

Clinical studies of sulfamethoxazole and trimethoprim oral suspension did not include sufficient numbers of subjects aged 65 and over to determine whether they respond differently from younger subjects.

There may be an increased risk of severe adverse reactions in elderly patients, particularly when complicating conditions exist, e.g., impaired kidney and/or liver function, possible folate deficiency, or concomitant use of other drugs. Severe skin reactions, generalized bone marrow suppression (see WARNINGSand ADVERSE REACTIONS), a specific decrease in platelets (with or without purpura), and hyperkalemia are the most frequently reported severe adverse reaction in elderly patients. In those concurrently receiving certain diuretics, primarily thiazides, an increased incidence of thrombocytopenia with purpura has been reported. Increased digoxin blood levels can occur with concomitant sulfamethoxazole and trimethoprim therapy, especially in elderly patients. Serum digoxin levels should be monitored. Hematological changes indicative of folic acid deficiency may occur in elderly patients. These effects are reversible by folinic acid therapy. Appropriate dosage adjustments should be made for patients with impaired kidney function and duration of use should be as short as possible to minimize risks of undesired reactions (see DOSAGE AND ADMINISTRATION). The trimethoprim component of this product may cause hyperkalemia when administered to patients with underlying disorders of potassium metabolism, with renal insufficiency, or when given concomitantly with drugs known to induce hyperkalemia, such as angiotensin converting enzyme inhibitors. Close monitoring of serum potassium is warranted in these patients. Discontinuation of sulfamethoxazole and trimethoprim treatment is recommended to help lower potassium serum levels.

Pharmacokinetics parameters for sulfamethoxazole were similar for geriatric subjects and younger adult subjects. The mean maximum serum trimethoprim concentration was higher and mean renal clearance of trimethoprim was lower in geriatric subjects compared with younger subjects^3 (see CLINICAL PHARMACOLOGY, Geriatric Pharmacokinetics).

ADVERSE REACTIONS

The most common adverse effects are gastrointestinal disturbances (nausea, vomiting, anorexia) and allergic skin reactions (such as rash and urticaria). FATALITIES ASSOCIATED WITH THE ADMINISTRATION OF SULFONAMIDES, ALTHOUGH RARE, HAVE OCCURRED DUE TO SEVERE REACTIONS, INCLUDING STEVENS-JOHNSON SYNDROME, TOXIC EPIDERMAL NECROLYSIS, FULMINANT HEPATIC NECROSIS, AGRANULOCYTOSIS, APLASTIC ANEMIA, OTHER BLOOD DYSCRASIAS, AND HYPERSENSITIVITY OF THE RESPIRATORY TRACT (SEE WARNINGS).

Hematologic

Agranulocytosis, aplastic anemia, thrombocytopenia, leukopenia, neutropenia, hemolytic anemia, megaloblastic anemia, hypoprothrombinemia, methemoglobinemia, eosinophilia.

Allergic

Stevens-Johnson syndrome, toxic epidermal necrolysis, anaphylaxis, allergic myocarditis, erythema multiforme, exfoliative dermatitis, angioedema, drug fever, chills, Henoch-Schönlein purpura, serum sickness-like syndrome, generalized allergic reactions, generalized skin eruptions, photosensitivity, conjunctival and scleral injection, pruritus, urticaria, and rash. In addition, periarteritis nodosa and systemic lupus erythematosus have been reported.

Gastrointestinal

Hepatitis, including cholestatic jaundice and hepatic necrosis, elevation of serum transaminase and bilirubin, pseudomembranous enterocolitis, pancreatitis, stomatitis, glossitis, nausea, emesis, abdominal pain, diarrhea, anorexia.

Genitourinary

Renal failure, interstitial nephritis, BUN and serum creatinine elevation, toxic nephrosis with oliguria and anuria, and crystalluria.

Metabolic

Hyperkalemia, hyponatremia.

Neurologic

Aseptic meningitis, convulsions, peripheral neuritis, ataxia, vertigo, tinnitus, headache.

Psychiatric

Hallucinations, depression, apathy, nervousness.

Endocrine

The sulfonamides bear certain chemical similarities to some goitrogens, diuretics (acetazolamide and the thiazides), and oral hypoglycemic agents. Cross-sensitivity may exist with these agents. Diuresis and hypoglycemia have occurred rarely in patients receiving sulfonamides.

Musculoskeletal

Arthralgia and myalgia.

Respiratory System

Cough, shortness of breath, and pulmonary infiltrates (see WARNINGS).

Miscellaneous

Weakness, fatigue, insomnia.

OVERDOSAGE

Acute

The amount of a single dose of sulfamethoxazole and trimethoprim that is either associated with symptoms of overdosage or is likely to be life-threatening has not been reported. Signs and symptoms of overdosage reported with sulfonamides include anorexia, colic, nausea, vomiting, dizziness, headache, drowsiness and unconsciousness. Pyrexia, hematuria, and crystalluria may be noted. Blood dyscrasias and jaundice are potential late manifestations of overdosage. Signs of acute overdosage with trimethoprim include nausea, vomiting, dizziness, headache, mental depression, confusion and bone marrow depression. General principles of treatment include the institution of gastric lavage or emesis; forcing oral fluids; and the administration of intravenous fluids if urine output is low and renal function is normal. Acidification of the urine will increase renal elimination of trimethoprim. The patient should be monitored with blood counts and appropriate blood chemistries, including electrolytes. If a significant blood dyscrasia or jaundice occurs, specific therapy should be instituted for these complications. Peritoneal dialysis is not effective and hemodialysis is only moderately effective in eliminating trimethoprim and sulfamethoxazole.

Chronic

Use of sulfamethoxazole and trimethoprim at high doses and/or for extended periods of time may cause bone marrow depression manifested as thrombocytopenia, leukopenia, and/or megaloblastic anemia. If signs of bone marrow depression occur, the patient should be given leucovorin; 5 to 15 mg leucovorin daily has been recommended by some investigators.

DOSAGE AND ADMINISTRATION

Contraindicated in pediatric patients less than 2 months of age.

Urinary Tract Infections and Shigellosis in Adults and Pediatric Patients and Acute Otitis Media in Pediatric Patients

Adults

The usual adult dosage in the treatment of urinary tract infections is four teaspoonfuls (20mL) Sulfamethoxazole and trimethoprim oral suspension every 12 hours for 10 to 14 days. An identical daily dosage is used for 5 days in treatment of shigellosis.

Pediatric Patients

The recommended dose for pediatric patients with urinary tract infections or acute otitis media is 40 mg/kg sulfamethoxazole and 8 mg/kg trimethoprim per 24 hours, given in two divided doses every 12 hours for 10 days. An identical daily dosage is used for 5 days in the treatment of shigellosis. The following table is a guideline for the attainment of this dosage:

Pediatric Patients Two months of age or older:

Weight |  | Dose - Every 12 hours
lb | kg | Teaspoonfuls
22 | 10 | 1 | (5 mL)
44 | 20 | 2 | (10 mL)
66 | 30 | 3 | (15 mL)
88 | 40 | 4 | (20 mL)

For Patients with Impaired Renal Function: When renal function is impaired, a reduced dosage should be employed using the following table:

Creatinine Clearance (mL/min) | Recommended Dosage Regimen
Above 30 | Use Standard Regimen
15 - 30 | 1/2 the Usual Regimen
Below 15 | Use Not Recommended

Acute Exacerbations of Chronic Bronchitis in Adults

The usual adult dosage in the treatment of acute exacerbations of chronic bronchitis is four teaspoonfuls (20 mL) sulfamethoxazole and trimethoprim oral suspension every 12 hours for 14 days.

Travelers’ Diarrhea in Adults

For the treatment of travelers' diarrhea, the usual adult dosage is four teaspoonfuls (20mL) of sulfamethoxazole and trimethoprim oral suspension every 12 hours for 5 days.

Pneumocystis Carinii Pneumonia

Treatment

Adults and Pediatric Patients: The recommended dosage for treatment of patients with documented Pneumocystis carinii pneumonia is 75 to 100 mg/kg sulfamethoxazole and 15 to 20 mg/kg trimethoprim per 24 hours given in equally divided doses every 6 hours for 14 to 21 days. The following table is a guideline for the upper limit of this dosage:

Weight |  | Dose - Every 6 Hours
lb | kg | Teaspoonfuls
18 | 8 | 1 | (5 mL)
35 | 16 | 2 | (10 mL)
53 | 24 | 3 | (15 mL)
70 | 32 | 4 | (20 mL)
88 | 40 | 5 | (25 mL)
106 | 48 | 6 | (30 mL)
141 | 64 | 8 | (40 mL)
176 | 80 | 10 | (50 mL)

For the lower limit dose (75 mg/kg sulfamethoxazole and 15 mg/kg trimethoprim per 24 hours) administer 75% of the dose in the above table.

Prophylaxis

Adults

The recommended dosage for prophylaxis in adults is four teaspoonfuls (20 mL) of the suspension daily.

Pediatric Patients

For pediatric patients, the recommended dose is 750 mg/m^2/day sulfamethoxazole with 150 mg/m^2/day trimethoprim given orally in equally divided doses twice a day, on 3 consecutive days per week. The total daily dose should not exceed 1,600 mg sulfamethoxazole and 320 mg trimethoprim. The following table is a guideline for the attainment of this dosage in pediatric patients:

Body Surface Area | Dose - Every 12 Hours
(m^2) | Teaspoonfuls
0.26 | 1/2 | (2.5 mL)
0.53 | 1 | (5 mL)
1.06 | 2 | (10 mL)

HOW SUPPLIED

Sulfamethoxazole and Trimethoprim Oral Suspension, USP is supplied in a purple grape-flavored suspension and in a pink cherry-flavored suspension containing 40 mg trimethoprim and 200 mg sulfamethoxazole per 5 mL (teaspoonful) both packaged in 1 pint (473 mL) bottles.

Store at 20°-25°C (68°-77°F) [see USP Controlled Room Temperature]. Protect from light.

Dispense in a tight, light-resistant container as defined in the USP, with a child-resistant closure (as required).

To report SUSPECTED ADVERSE REACTIONS, contact Hi-Tech Pharmacal Co., Inc. at 1-800-262-9010 or FDA at 1-800-FDA-1088 or www.fda.gov/medwatch.

Rx Only

REFERENCES

1. Kremers P, Duvivier J, Heusghem C. Pharmacokinetic Studies of Co-Trimoxazole in Man after Single and Repeated Doses. J Clin Pharmacol. 1974; 14:112-117.
2. Kaplan SA, Weinfeld RE, Abruzzo CW, McFaden K, Jack ML, Weissman L. Pharmacokinetic Profile of Trimethoprim-Sulfamethoxazole in Man. J Infect Dis. 1973; 128 (Suppl): S547-S555.
3. Varoquaux, O, et al. Antibiotic Susceptibility Discs; Certification Procedure. Federal Register. 1972; 37:20527-20529.
4. Bauer AW, Kirby WMM, Sherris JC, Turck M. Antibiotic Susceptibility Testing by Standardized Single Disk Method. Am J Clin Pathol. 1966; 45:493-496.
5. Brumfitt W, Pursell R. Trimethoprim-Sulfamethoxazole in the Treatment of Bacteriuria in Women. J Infect Dis. 1973; 128 (Suppl):S657-S663.
6. Marinella MA. Trimethoprim-Induced Hyperkalemia: An Analysis of Reported Cases. Gerontology 45:209-212, 1999.

Manufactured by:

Hi-Tech Pharmacal Co., Inc.

Amityville, NY 11701

Rev. 823/824:05 10/09

CR #1115

Repackaged by:

Rebel Distributors Corp

Thousand Oaks, CA 91320